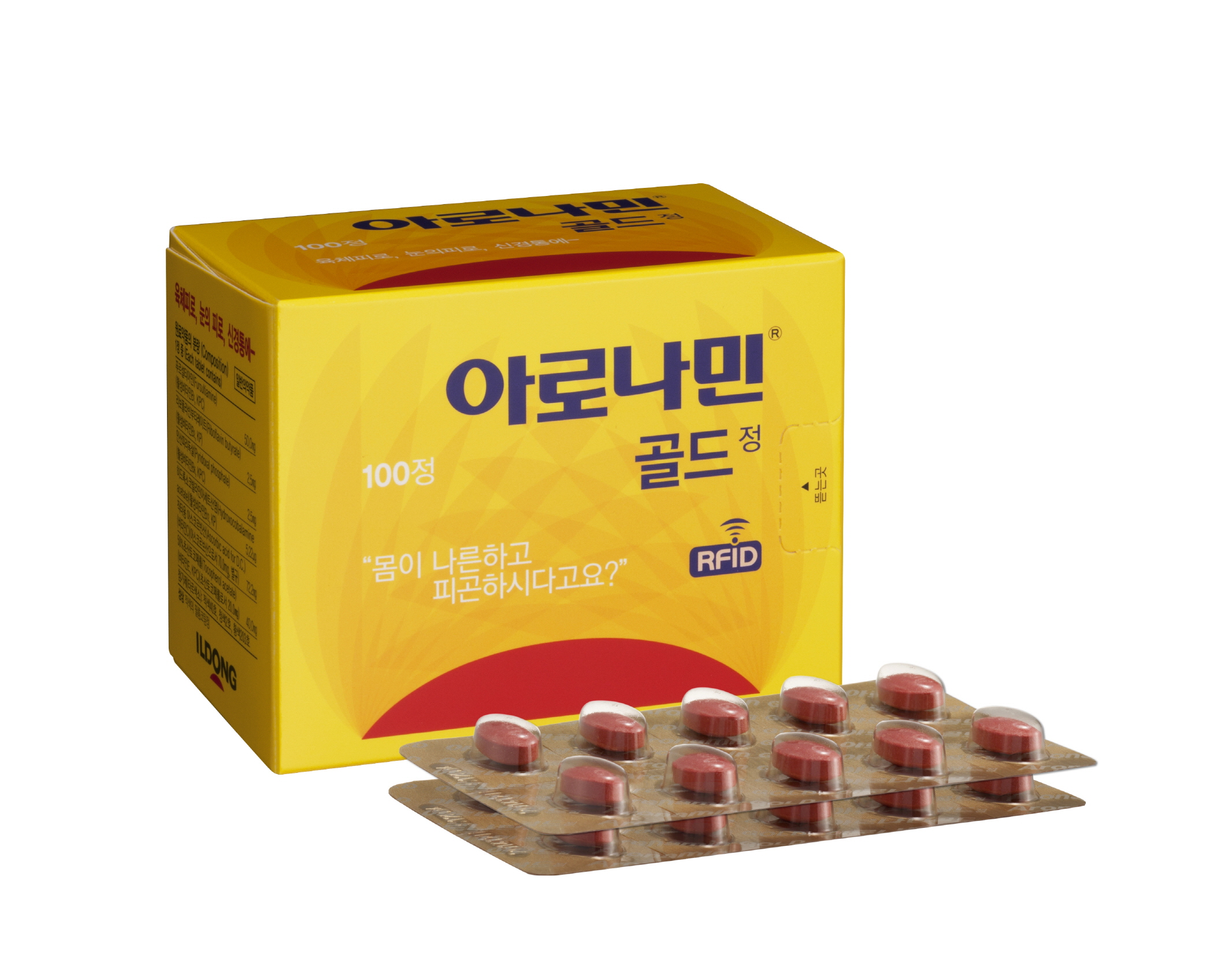 DRUG LABEL: ARONAMIN GOLD
NDC: 72689-0024 | Form: TABLET, FILM COATED
Manufacturer: OASIS TRADING
Category: otc | Type: HUMAN OTC DRUG LABEL
Date: 20181212

ACTIVE INGREDIENTS: RIBOFLAVIN TETRABUTYRATE 2.5 mg/1 1; FURSULTIAMINE 50 mg/1 1; HYDROXOCOBALAMIN ACETATE 5.22 ug/1 1; .ALPHA.-TOCOPHEROL ACETATE 20 mg/1 1; ASCORBIC ACID 70 mg/1 1
INACTIVE INGREDIENTS: LACTOSE MONOHYDRATE; MAGNESIUM STEARATE; MICROCRYSTALLINE CELLULOSE; COPOVIDONE K25-31; SILICON DIOXIDE; CROSPOVIDONE

Fursultiamine(Active vitamin B1) 50.0mg
Riboflavin tetrabutyrate(Active vitamin B2) 2.5mg
Pyridoxal phosphate(Active vitamin B6) 2.5mg
Hydroxocobalamin acetate(Active vitamin B12) 5.22μg
Ascorbic acid(Vitamin C) 70mg
Tocopheryl acetate(Vitamin E) 20.0mg

PURPOSE

Vitamines, Mineral & nutrients

Keep out of reach of children

INDICATIONS AND USAGE

Adults: take 1 tablet twice a day.

WARNINGS

1) Do not take this medicine.

(1) Patients with hypersensitivity reactions to NSAIDs and the components contained in NSAIDs

(2) Infants under three months of age

(3) Because this drug contains lactose, patients with genetic problems such as galactose intolerance, Lapp lactase deficiency, or glucose-galactose malabsorption Do not administer.

2) Do not take the following medicine while taking this medicine.

(1) levodopa

3) Consult a doctor, dentist or pharmacist before taking this medicine.

(1) Patients receiving medical treatment

(2) patients with hyperoxaluria (excessive urinary excretion of urine)

(3) Pregnant women and possibly pregnant women, lactating women, premature infants, infants

(4) Patients with gout or kidney stones

4) Stop taking this drug immediately and consult a doctor, dentist, or pharmacist if you: Whenever possible, bring this attached document with you.

(1) If you have any of the following symptoms

Stomach discomfort, diarrhea, constipation, rash, fever, nausea, vomiting, dilated stool, stomatitis (mouth salt), anorexia, abdominal bloating

(2) Administration of this drug may result in faster or more frequent menstruation, and bleeding may last for a long time.

(3) The risk of thrombosis may be increased if a woman taking an oral contraceptive containing estrogen or a patient with thrombotic placenta is taking vitamin E.

(4) Long-term administration of high doses may result in resistance.

(5) Prolonged use of pyridoxine at a dose of 500 mg to 2 g / day may result in neuropathy or neuropathy (functional disorder or pathologic changes) in the peripheral nervous system.

(6) Hematologic adverse events may occur when vitamin B12 is administered at a dose of 10 μg or more per day in patients with insufficient folic acid.

5) Other Precautions for Taking

(1) Keep the prescribed dosage and dosage.

(2) it may interfere with the detection of blood glucose during various urine tests

(3) The urine may turn yellow, which may affect the clinical examination

6) Storage Precautions

(1) Keep out of the reach of children.

(2) Avoid direct sunlight. Store in a cool, dry place.

(3) To prevent misuse (misuse) and to preserve quality, please do not put in another container.

INACTIVE INGREDIENT

Microcrystalline Cellulose, Magnesium Stearate, Crospovidone, Copovidone, Colloidal Silicon Dioxide, OY-25014, OY-S-29019

DOSAGE AND ADMINISTRATION

For oral use only